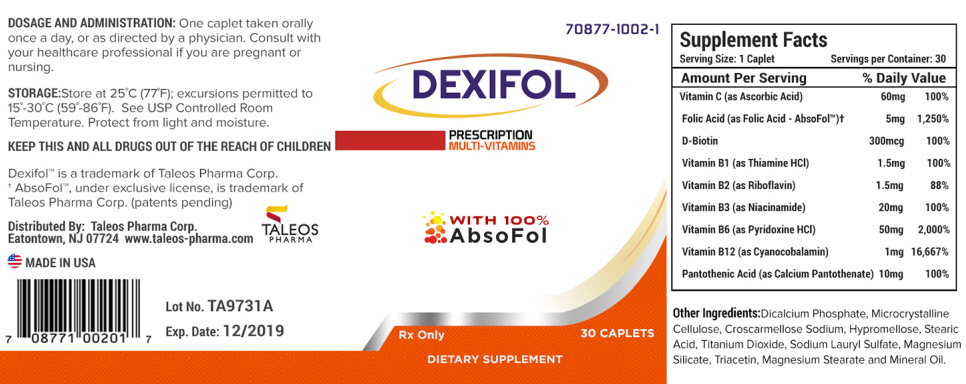 DRUG LABEL: DEXIFOL
NDC: 70877-1002 | Form: TABLET, FILM COATED
Manufacturer: Taleos Pharma
Category: other | Type: DIETARY SUPPLEMENT
Date: 20180105

ACTIVE INGREDIENTS: Ascorbic Acid 60 mg/1 1; Folic Acid 5 mg/1 1; Biotin 300 ug/1 1; Thiamine Hydrochloride 1.5 mg/1 1; Riboflavin 1.5 mg/1 1; Niacinamide 20 mg/1 1; Pyridoxine Hydrochloride 50 mg/1 1; Cyanocobalamin 1 mg/1 1; Calcium Pantothenate 10 mg/1 1
INACTIVE INGREDIENTS: ANHYDROUS DIBASIC CALCIUM PHOSPHATE; Microcrystalline Cellulose; Croscarmellose Sodium; Hypromellose 2910 (15 mpa.s); Stearic Acid; Titanium Dioxide; Sodium Lauryl Sulfate; Magnesium Silicate; Triacetin; Magnesium Stearate; Mineral Oil

DEXIFOL Caplets

HEALTH CLAIM

Rx Only

DESCRIPTION

DEXIFOL is a prescription multi-vitamin in the form of a dark yellow, film-coated, caplet.

INDICATION AND USAGE

DEXIFOL is a prescription multi-vitamin supplement that can be taken to improve nutritional status in conditions requiring dietary supplementation. DEXIFOL can also be used for the dietary management of individuals with distinct nutritional needs under a physician or healthcare provider's supervision for end stage failure, dialysis, hyperhomocysteinemia or inadequate dietary vitamin intake.

CONTRAINDICATIONS

This product is contraindicated in patients with a known hypersensitivity to any of the ingredients.

WARNING

Folic Acid in doses above 0.1 mg daily may obscure pernicious anemia in that hematological remission can occur while neurological manifestations remain progressive. Folic Acid alone is improper therapy in the treatment of pernicious anemia and other megaloblastic anemias where vitamin B12 is deficient.

DO NOT EXCEED RECOMMENDED DOSAGE.

KEEP THIS AND ALL MEDICATIONS OUT OF THE REACH OF CHILDREN.

PRECAUTIONS

Folic Acid in doses above 0.1 mg daily may obscure pernicious anemia in that hematological remission can occur while neurological manifestations remain progressive. The 1 mg of cyanocobalamin contained in DEXIFOL Caplets has been shown to provide an adequate amount of cyanocobalamin to address this precaution. A safer upper limit of 100 mg per day has been established for the unsupervised medical use of pyridoxine. Consider all sources of pyridoxine supplementation when prescribing DEXIFOL Caplets.

If pregnant, or planning to become pregnant or are currently breast-feeding please contact your physician, or healthcare provider before using or continuing use of this medication.

ADVERSE REACTIONS

Allergic sensitization has been reported following both oral and parenteral administration of folic acid. Paresthesia and somnolence have been reported with the use of pyridoxine hydrochloride. Mild transient diarrhea, polycynthemia vera, peripheral vascular thrombosis, itching transitory exanthema and feeling of swelling of the entire body has been associated with the use of cyanocobalamin.

DRUG INTERACTIONS

Pyridoxine supplements should not be given to patients receiving the drug levodopa, because the action of levodopa is antagonized by pyridoxine. However, pyridoxine may be used concurrently in patients receiving a preparation containing both carbidopa and levodopa. Concurrent use of phenytoin and folacin (folic acid) may result in decreased phenytoin effectiveness.

DOSAGE AND ADMINISTRATION

Adults

One caplet taken orally daily or as directed by a physician.

DO NOT EXCEED RECOMMENDED DOSAGE.

STATEMENT OF IDENTITY

Supplement Facts
Serving Size: 1 Caplet | Servings per Container: 30
Amount Per Serving | % Daily Value
Vitamin C (as Ascorbic Acid) | 60mg | 100%
Folic Acid (as Folic Acid - AbsoFol™) [AbsoFol™, under exclusive license, is trademark of Taleos Pharma Corp. (patents pending) DEXIFOL and TALEOS are trademarks of Taleos Pharma Corp.] | 5mg | 1,250%
D-Biotin | 300mcg | 100%
Vitamin B1 (as Thiamine HCl) | 1.5mg | 100%
Vitamin B2 (as Riboflavin) | 1.5mg | 88%
Vitamin B3 (as Niacinamide) | 20mg | 100%
Vitamin B6 (as Pyridoxine HCl) | 50mg | 2,000%
Vitamin B12 (as Cyanocobalamin) | 1mg | 16,667%
Pantothenic Acid (as Calcium Pantothenate) | 10mg | 100%

STORAGE

Store at 20° - 25°C (68° - 77°F); excursions permitted to 15° - 30°C (59° - 86°F) [See USP Controlled Room Temperature.]

Protect from light and moisture.
Dispense in a well-closed, tight, light-resistant container as defined by the USP using a child resistant closure.

HOW SUPPLIED

DEXIFOL caplets are supplied as dark yellow, oblong, film coated caplets. DEXIFOL caplets are available in bottles of 30 (NDC: 70877-1002-01).

HEALTH CLAIM

Distributed By:
Taleos Pharma Corp.
Eatontown, NJ 07724
www.taleos-pharma.com

PRINCIPAL DISPLAY PANEL - 30 Caplet Bottle Label

70877-1002-1

DEXIFOL

PRESCRIPTION
MULTI-VITAMINS

WITH 100%
AbsoFol

Rx Only
30 CAPLETS

DIETARY SUPPLEMENT